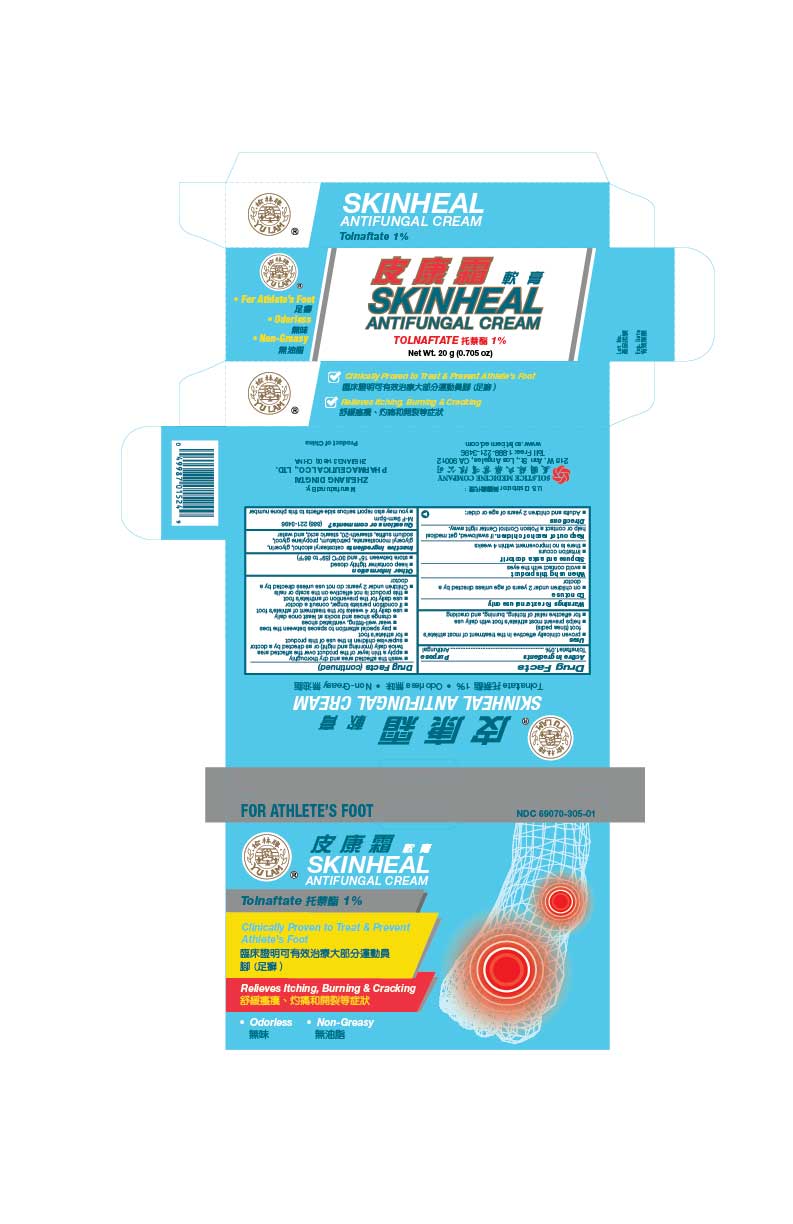 DRUG LABEL: SKINHEAL ANTIFUNGAL
NDC: 69070-305 | Form: CREAM
Manufacturer: Zhejiang Dingtai Pharmaceutical Co., Ltd
Category: otc | Type: HUMAN OTC DRUG LABEL
Date: 20251110

ACTIVE INGREDIENTS: TOLNAFTATE 1 g/100 g
INACTIVE INGREDIENTS: CETOSTEARYL ALCOHOL; GLYCERIN; GLYCERYL MONOSTEARATE; PETROLATUM; PROPYLENE GLYCOL; SODIUM SULFITE; STEARETH-20; STEARIC ACID; WATER

Drug Facts

Active ingredient
Tolnaftate 1.0%

Purpose
Antifungal

Uses
proven clinically effective in the treatment of most athlete’s foot (tinea pedis) and ringworm (tinea corporis)
helps prevent most athlete’s foot with daily use for effective relief of itching, burning, and cracking

Warnings
For external use only

Do not use
on children under 2 years of age unless directed by a doctor

When using this product
avoid contact with the eyes

Stop use and ask a doctor if
irritation occurs
there is no improvement within 4 weeks

Keep out of reach of children.If swallowed, get medical help or contact a Poison Control Center right away.

Directions
Adults and children 2 years of age or older:
wash the affected area and dry thoroughly
apply a thin layer of the product over the affected area twice daily (morning and night) or as directed by a doctor
supervise children in the use of this product
for athlete’s foot
pay special attention to spaces between the toes
wear well-fitting, ventilated shoes
change shoes and socks at least once daily
use daily for 4 weeks for the treatment of athlete’s foot and ringworm
if condition persists longer, consult a doctor
use daily for the prevention of athlete’s foot
this product is not effective on the scalp or nails
Children under 2 years: do not use unless directed by a doctor

Other information
keep container tightly closed
store between 15 and 30 C (59 to 86 F)

INACTIVE INGREDIENT

Inactive ingredients cetostearyl alcohol, glycerin, glyceryl monostearate, petrolatum, propylene glycol, sodium sulfite, steareth- 20, stearic acid, and water

Questions or comments?(888) 221-3496 M-F 9am-5pm
you may also report serious side effects to this phone number

PACKAGE LABEL

SKINHEAL ANTIFUNGAL CREAM
Tolnaftate 1%
Net Wt. 10 g (1/3 oz)
NDC 69070-305-01